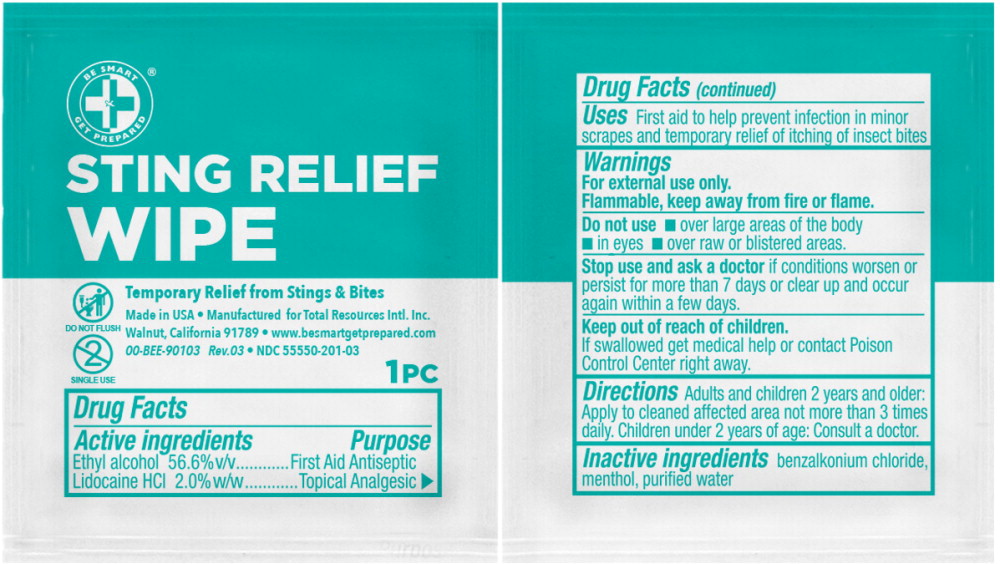 DRUG LABEL: Be Smart Get Prepared Sting Relief  Wipe
NDC: 55550-201 | Form: LIQUID
Manufacturer: Total Resources International, Inc
Category: otc | Type: HUMAN OTC DRUG LABEL
Date: 20251009

ACTIVE INGREDIENTS: Alcohol 0.566 mL/1 mL; LIDOCAINE HYDROCHLORIDE 20 mg/1 mL
INACTIVE INGREDIENTS: benzalkonium chloride; menthol; water

Drug Facts

Active Ingredients

Ethyl alcohol 56.6% v/v

Lidocaine HCl 2.0% w/w

Purpose

First Aid Antiseptic

Topical Analgesic

Uses

First aid to help prevent infection in minor scrapes and temporary relief of itching of insect bites

Warnings

For external use only.

Flammable, keep away from fire or flame.

Do not use

- over large areas of the body
- in eyes
- over raw or blistered areas

Stop use and ask doctor if conditions worsen or persist for more than 7 days or clear up and occur again within a few days.

Keep out of reach of children

If swallowed get medical help or contact a Poison Control Center right away

Directions

Adults and children 2 years and older: Apply to cleaned affected area not more than 3 times daily. Children under 2 years of age: Consult a doctor.

Inactive ingredients

benzalkonium chloride, menthol, purified water

Principal Display Panel – 0.8 g Pouch Label

BE SMART®

GET PREPARED

STING RELIEF
WIPE

DO NOT FLUSH

SINGLE USE

Temporary Relief from Stings & Bites

Made in USA • Manufactured forTotal Resources Inti. Inc.

Walnut, California 91789 • www.besmartgetprepared.com

00-BEE-90103 Rev.03 • NDC 55550-201 -03

1PC